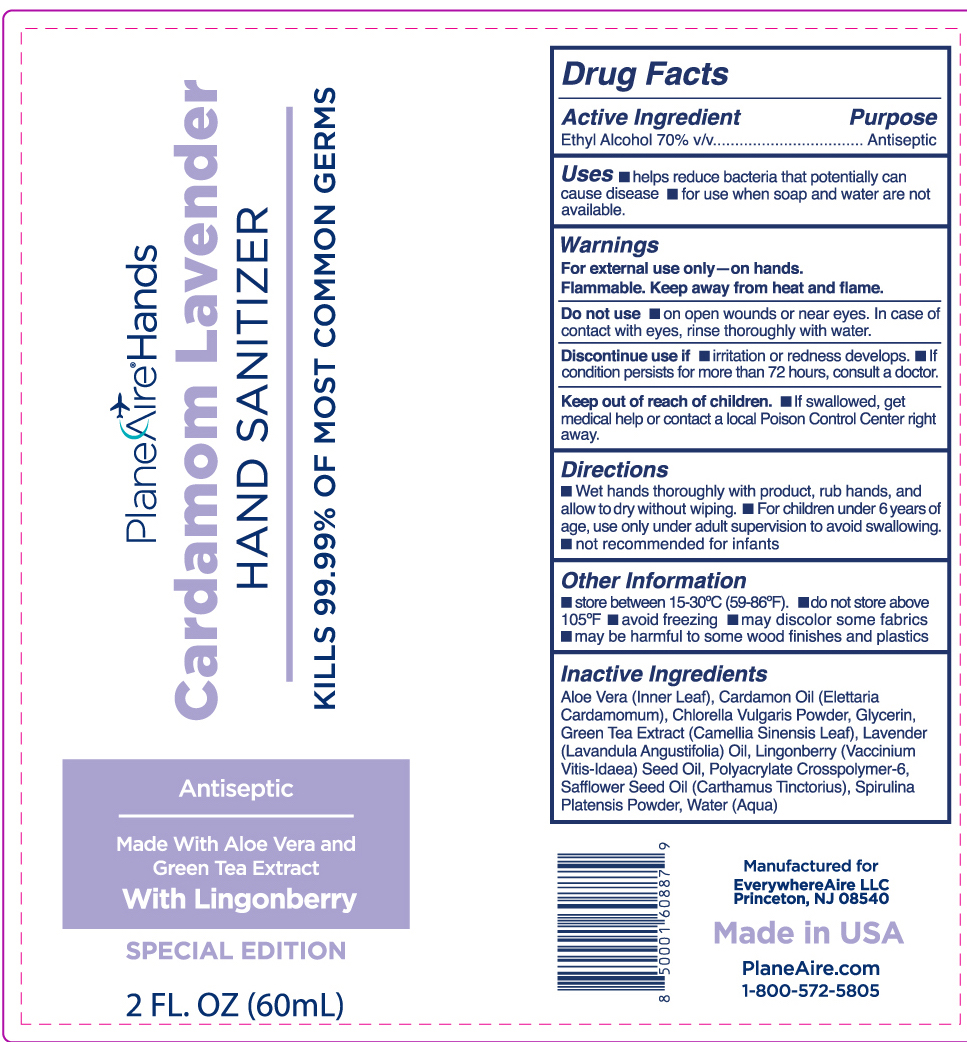 DRUG LABEL: PlaneAire Hands hand sanitizer
NDC: 80335-115 | Form: LOTION
Manufacturer: EverywhereAire LLC
Category: otc | Type: HUMAN OTC DRUG LABEL
Date: 20231220

ACTIVE INGREDIENTS: ALCOHOL 70 mL/100 mL
INACTIVE INGREDIENTS: CARTHAMUS TINCTORIUS (SAFFLOWER) OLEOSOMES; SODIUM POLYACRYLATE (2500000 MW); CHLORELLA VULGARIS; SPIRULINA PLATENSIS; GREEN TEA LEAF; CARDAMOM OIL; ALOE VERA LEAF POLYSACCHARIDES; LINGONBERRY SEED OIL; GLYCERIN; WATER; LAVENDER OIL

PlaneAire Hands lotion cardamom lavender with chlorella spirulina and safflower oil

Active Ingredient

Ethyl Alcohol 70% v/v

Purpose

Antiseptic

Uses

- helps reduce bacteria that potentially can cause disease
- for use when soap and water are not available

Uses

Sectiin category updated

Warnings

- For external us eonly- on hands.
- Flammable. Keep away from heat and flame

Do not use

- on open wounds or near eyes. In case of contact with eyes, rinse thoroughly with water.

Discontinue use if

- irritation or redness develops
- If condition persists for more than 72 hours, consult a doctor

Keep out of reach of children

- If swallowed, get medical help or contact a local Poison Control Center right away

Directions

- Wet hands thoroughly with product, rub hands, and allow to dry without wiping.
- For children under 6 years of age, use only under adult supervision to avoid swallowing.
- not recommended for infants

Other Information

- store between 15-30C (59-86F)
- do not store above 105F
- avoid freezing
- may discolor fabrics
- may be harmful to some wood finishes and plastics

Inactive Ingredients

Aloe Vera (Inner Leaf),Cardamom Oil (Elettaria Cardamomum), Chlorella Vulgaris Powder, Glycerin, Green Tea Extract (Camellia Sinensis Leaf), Lavender (Lavandula Angustifolia) Oil, Lingonberry (Vaccinium Vitis-Idaea) Seed Oil, Polyacrylate Crosspolymer-6, Safflower Seed Oil (Carthamus Tinctorius), Spirulina Platensis Powder, Water (Aqua)